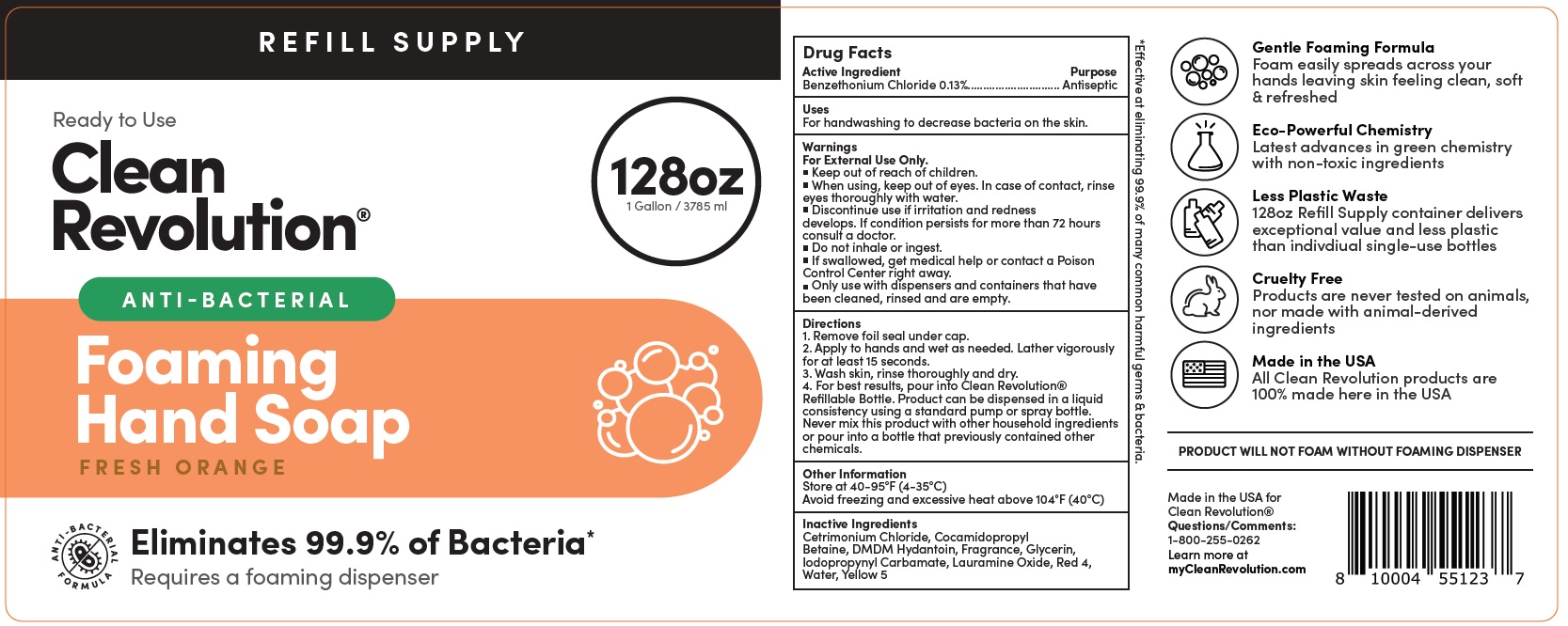 DRUG LABEL: Clean Revolution Anti-Bacterial Foaming Hand Refill Supply Container - Anti-Bacterial - ELIMINATES 99.9% Germs - Ready To Use - Fresh Orange
NDC: 74810-727 | Form: LIQUID
Manufacturer: Replenish Bottling LLC
Category: otc | Type: HUMAN OTC DRUG LABEL
Date: 20231226

ACTIVE INGREDIENTS: BENZETHONIUM CHLORIDE 1.3 mg/1 mL
INACTIVE INGREDIENTS: CETRIMONIUM CHLORIDE; COCAMIDOPROPYL BETAINE; DMDM HYDANTOIN; GLYCERIN; LAURAMINE OXIDE; FD&C RED NO. 4; WATER; FD&C YELLOW NO. 5

Clean Revolution Anti-Bacterial Foaming Hand Soap Refill Supply Container | Anti-Bacterial | ELIMINATES 99.9% Germs | Ready To Use | Fresh Orange

Active Ingredient

Benzethonium Chloride 0.13%

Purpose

Antiseptic

Uses

For handwashing to decrease bacteria on the skin.

Warnings

For External Use Only.

When using,

- keep out of eyes. In case of contact, rinse eyes thoroughly with water.
- Discontinue use if irritation and redness develops. If condition persists for more than 72 hours consult a doctor.
- Do not inhale or ingest.
- If swallowed, get medical help or contact a Poison Control Center right away.
- Only use with dispensers and containers that have been cleaned, rinsed and are empty.

Directions

1. Remove foil seal under cap.
2. Apply to hands and wet as needed. Lather vigorously for at least 15 seconds.
3. Wash skin, rinse thoroughly and dry.
4. For best results, pour into Clean Revolution® Refillable Bottle. Product can be dispensed in a liquid consistency using a standard pump or spray bottle. Never mix this product with other household ingredients or pour into a bottle that previously contained other chemicals.

Other Information

Store at 40-95°F (4-35°C)
Avoid freezing and excessive heat above 104°F (40°C)

Inactive Ingredients

Cetrimonium Chloride, Cocamidopropyl Betaine, DMDM Hydantoin, Fragrance, Glycerin, Iodopropynyl Carbamate, Lauramine Oxide, Red 4, Water, Yellow 5